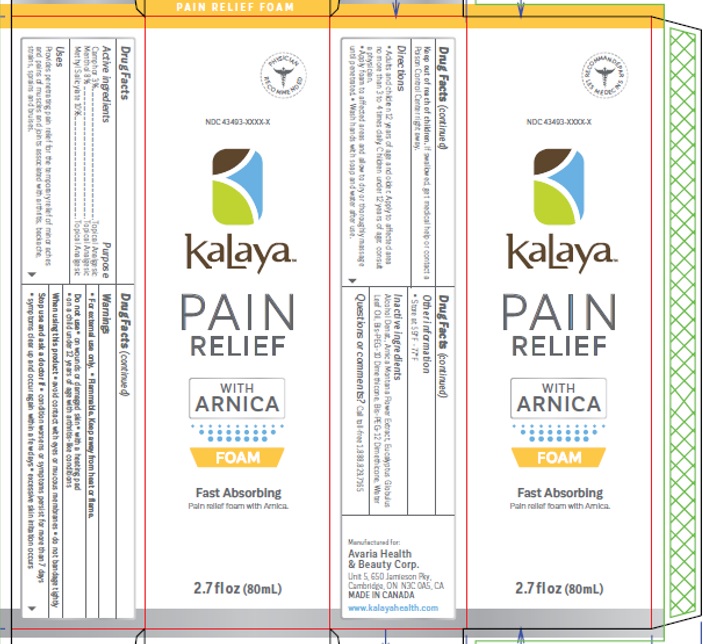 DRUG LABEL: KALAYA FOAMING PAIN RELIEF
NDC: 43493-0011 | Form: LIQUID
Manufacturer: Avaria Health & Beauty Corp
Category: otc | Type: HUMAN OTC DRUG LABEL
Date: 20251008

ACTIVE INGREDIENTS: METHYL SALICYLATE 10 g/100 mL; MENTHOL 8 g/100 mL; CAMPHOR (NATURAL) 3 g/100 mL
INACTIVE INGREDIENTS: ALCOHOL; ARNICA MONTANA WHOLE; BIS-PEG-12 DIMETHICONE (70 MPA.S); BIS-PEG-10 DIMETHICONE/DIMER DILINOLEATE COPOLYMER; WATER

Active ingredients

Camphor 3%
Menthol 8%
Methyl salicylate 10%

Purpose

Topical Analgesic

Uses

Provides penetrating pain relief for the temporary relief of minor aches and pains of muscles and joints

Warnings

For External Use Only. Flammable. Keep away from heat or flame.

Do not use:
• on wounds or damaged skin
• with a heating pad
• on a child under 12 years of age with arthritis-like conditions

When using this product avoid contact with eyes or mucous membranes, do not bandage tightly.

Stop use and ask a doctor if condition worsen or symptoms persist more than 7 days, symptoms clear up and occur again within a few days and/or excessive skin irritation occurs.

Keep out of reach of children
If swallowed, get medical help or contact a Poison Control Center right away

Directions

Adults and children 12 years and over: Spray evenly onto affected areas no more than 3 to 4 times daily. Apply spray to affected areas and

allowed to dry or thoroughly massage until penetrated. Wash hands with soap and water after use.

Other information

• Store at 59°F - 77°F

Inactive ingredients

Alcohol Denat., Arnica Montana Flower Extract, Bis-Peg 12 Dimethicone, Bis-Peg 10 Dimethicone, Water

Questions or comments?

Call toll-free 1.888.829.7165